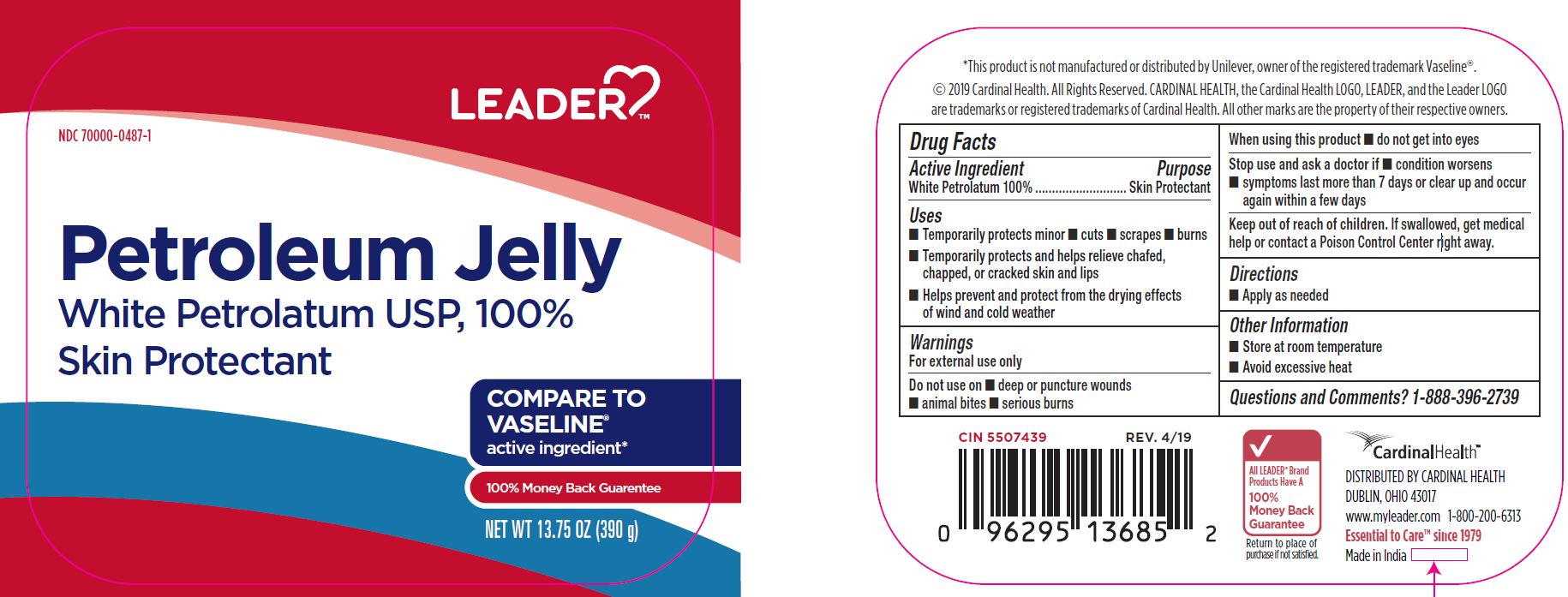 DRUG LABEL: White Petrolatum
NDC: 70000-0487 | Form: OINTMENT
Manufacturer: Cardinal Health
Category: otc | Type: HUMAN OTC DRUG LABEL
Date: 20251125

ACTIVE INGREDIENTS: PETROLATUM 1 g/1 g

CR-1147 White Petrolatum NDC 70000-0487-1

Active Ingredient

White Petrolatum 100%

Purpose

Skin Protectant

Uses

- Temporarily protects minor cuts, scrapes, burns
- Temporarily protects and helps relieve chafed, chapped, or cracked skin and lips
- Helps prevent and protect from the drying effects of wind and cold weather

Warnings

For external use only

Do not use on

- deep or puncture wounds
- animal bites
- serious burns

When using this product

do not get into eyes

Stop use and ask a doctor if

- condition worsens
- symptoms last more than 7 days or clear up and occur again within a few days

KEEP OUT OF REACH OF CHILDREN

If swallowed, get medical help or contact a Poison Control Center right away.

Directions

Apply as needed

Other Information

- Store at room temperature
- Avoid excessive heat

Questions and Comments

1-888-396-2739